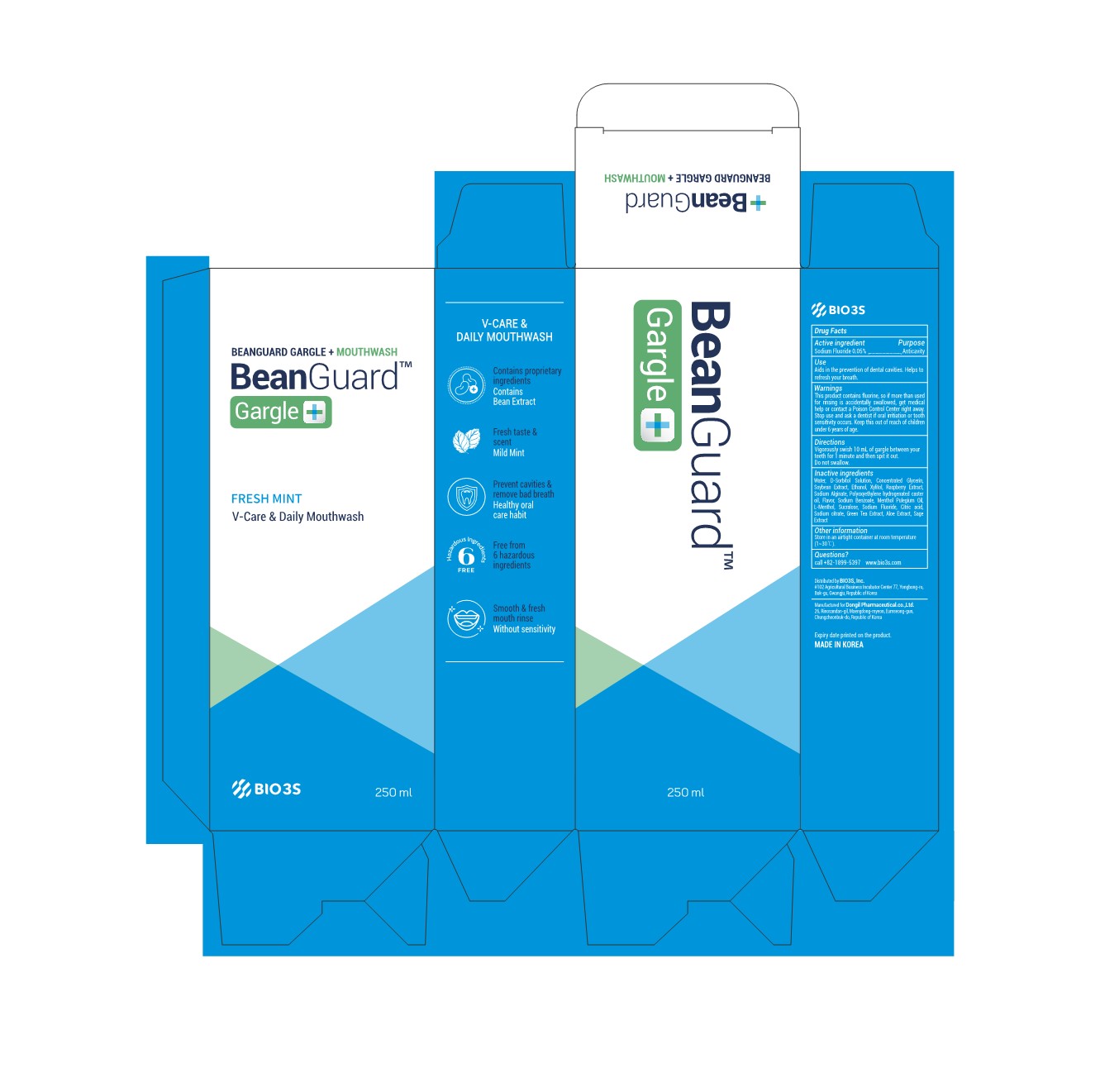 DRUG LABEL: Beanguard Gargle Plus
NDC: 77935-303 | Form: LIQUID
Manufacturer: BIO3S Co.,Ltd.
Category: otc | Type: HUMAN OTC DRUG LABEL
Date: 20220407

ACTIVE INGREDIENTS: SODIUM FLUORIDE 0.05 g/100 mL
INACTIVE INGREDIENTS: SOYBEAN; HYDROGENATED CASTOR OIL; PENNYROYAL OIL; MENTHOL, UNSPECIFIED FORM; SUCRALOSE; GREEN TEA LEAF; SODIUM BENZOATE; SORBITOL SOLUTION; GLYCERIN; XYLITOL; SODIUM ALGINATE; CITRIC ACID MONOHYDRATE; SODIUM CITRATE; ALOE; CLARY SAGE; WATER; ALCOHOL; RASPBERRY

77935-303 Beanguard Gargle Plus

Active Ingredient

Sodium Fluoride 0.05%

Purpose

Anticavity

Use

Aids in the prevention of dental cavities. Helps to refresh your breath.

Warnings

Do not use more or for longer than directed.

Warnings

This product contains fluorine, so if more than used for rinsing is accidentally swallowed, get medical help or contact a Poison Control Center right away.

Warnings

Stop use and ask a dentist if oral irritiation or tooth sensitivity occurs.

Warnings

Keep this out of reach of children under 6 years of age.

Inactive Ingredients

Water, D-Sorbitol Solution, Concentrated Glycerin, Soybean Extract, Ethanol, Xylitol, Raspberry Extract, Sodium Alginate, Polyoxyethylene hydrogenated caster oil, Flavor, Sodium Benzoate, Menthol Pulegium Oil, L-Menthol, Sucralose, Sodium Fluoride, Citric acid, Sodium citrate, Green Tea Extract, Aloe Extract, Sage Extract

Other Information

Store in an airtight container at room temperature (1~30℃).

Directions

Vigorously swish 10 mL of gargle between your teeth for 1 minute and then spit it out.
Do not swallow.

Warnings

Do not swallow.